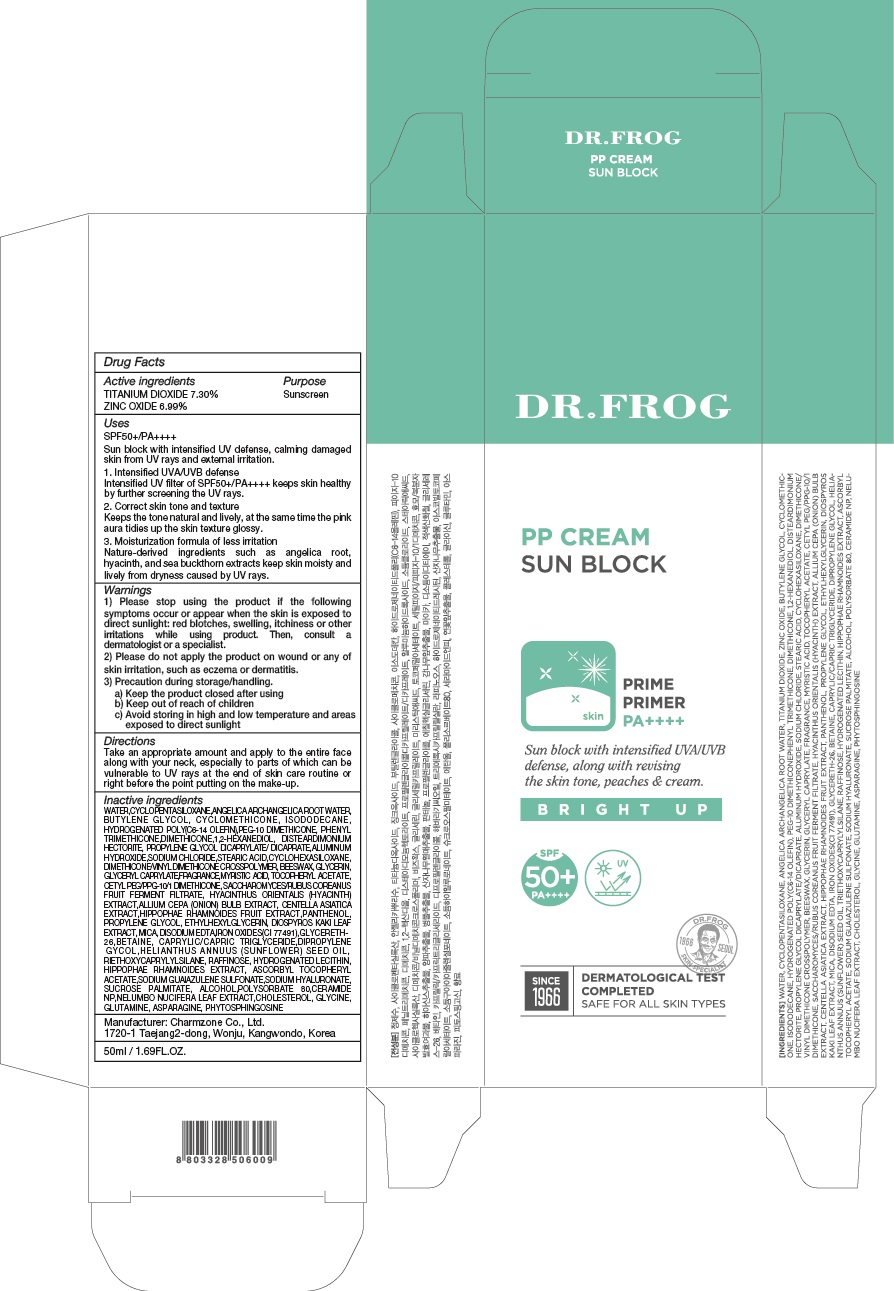 DRUG LABEL: DR FROG PP SUN BLOCK
NDC: 22201-1040 | Form: CREAM
Manufacturer: Charmzone Co Ltd
Category: otc | Type: HUMAN OTC DRUG LABEL
Date: 20180413

ACTIVE INGREDIENTS: TITANIUM DIOXIDE 3.65 g/50 mL; ZINC OXIDE 3.49 g/50 mL
INACTIVE INGREDIENTS: WATER; BUTYLENE GLYCOL

ACTIVE INGREDIENT

Active ingredients: TITANIUM DIOXIDE 7.30%, ZINC OXIDE 6.99%

INACTIVE INGREDIENT

Inactive ingredients:

WATER,CYCLOPENTASILOXANE,ANGELICA ARCHANGELICA ROOT WATER,BUTYLENE GLYCOL,CYCLOMETHICONE,ISODODECANE,HYDROGENATED POLY(C6-14 OLEFIN),PEG-10 DIMETHICONE, PHENYL TRIMETHICONE,DIMETHICONE,1,2-HEXANEDIOL,DISTEARDIMONIUM HECTORITE,PROPYLENE GLYCOL DICAPRYLATE/DICAPRATE,ALUMINUM HYDROXIDE,SODIUM CHLORIDE,STEARIC ACID,CYCLOHEXASILOXANE,DIMETHICONE/VINYL DIMETHICONE CROSSPOLYMER,BEESWAX,GLYCERIN,GLYCERYL CAPRYLATE,FRAGRANCE,MYRISTIC ACID,TOCOPHERYL ACETATE,CETYL PEG/PPG-10/1 DIMETHICONE,SACCHAROMYCES/RUBUS COREANUS FRUIT FERMENT FILTRATE,HYACINTHUS ORIENTALIS (HYACINTH) EXTRACT,ALLIUM CEPA (ONION) BULB EXTRACT,CENTELLA ASIATICA EXTRACT,HIPPOPHAE RHAMNOIDES FRUIT EXTRACT,PANTHENOL,PROPYLENE GLYCOL,ETHYLHEXYLGLYCERIN,DIOSPYROS KAKI LEAF EXTRACT,MICA,DISODIUM EDTA,IRON OXIDES(CI 77491),GLYCERETH-26,BETAINE,CAPRYLIC/CAPRIC TRIGLYCERIDE,DIPROPYLENE GLYCOL,HELIANTHUS ANNUUS (SUNFLOWER) SEED OIL,TRIETHOXYCAPRYLYLSILANE,RAFFINOSE,HYDROGENATED LECITHIN,HIPPOPHAE RHAMNOIDES EXTRACT,ASCORBYL TOCOPHERYL ACETATE,SODIUM GUAIAZULENE SULFONATE,SODIUM HYALURONATE,SUCROSE PALMITATE,ALCOHOL,POLYSORBATE 80,CERAMIDE NP,NELUMBO NUCIFERA LEAF EXTRACT,CHOLESTEROL,GLYCINE,GLUTAMINE,ASPARAGINE,PHYTOSPHINGOSINE

PURPOSE

Purpose: Sunscreen

WARNINGS

1) Please stop using the product if the following symptoms occur or appear when the skin is exposed to direct sunlight: red blotches, swelling, itchiness or other irritations while using product. Then, consult a dermatologist or a specialist.

2) Please do not apply the product on wound or any of skin irritation, such as eczema or dermatitis.

3) Precaution during storage/handling. a) Keep the product closed after using b) Keep out of reach of children c) Avoid storing in high and low temperature and areas exposed to direct sunlight

DESCRIPTION

Uses:

[UV PROTECTION]

SPF50+/PA++++

Sun block of Intensive UV defense along with natural toning up, enabling pink-shining and glossy skin.

1. Intensified UVA/UVB defense Intensified UV filter of SPF50+/PA++++ keeps skin healthy by further screening the UV rays.

2. Correct skin tone and texture Keeps the tone natural and lively, at the same time the pink aura tidies up the skin texture glossy.

3. Moisturization formula of less irritation Nature-derived ingredients such as angelica root, hyacinth, and sea buckthorn extracts keep skin moisty and lively from dryness caused by UV rays.

Directions:

Take an appropriate amount and apply to the entire face along with your neck, especially to parts of which can be vulnerable to UV rays at the end of skin care routine or right before the point putting on the make-up.